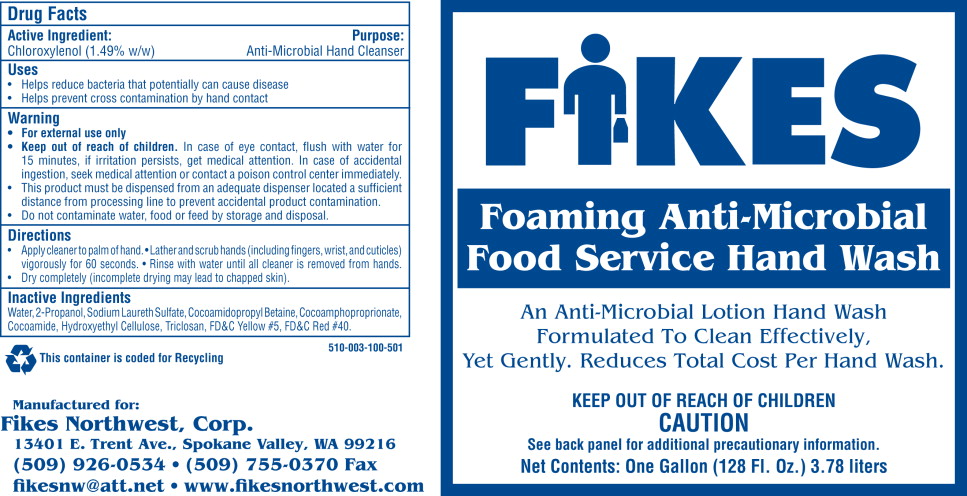 DRUG LABEL: FIKES Foaming Anti-Microbial Food Service Hand Wash
NDC: 50036-571 | Form: LIQUID
Manufacturer: Fikes Northwest, Corp.
Category: otc | Type: HUMAN OTC DRUG LABEL
Date: 20100903

ACTIVE INGREDIENTS: chloroxylenol 15.75 g/1000 mL
INACTIVE INGREDIENTS: water; sodium laureth sulfate; cocamidopropyl betaine; hydroxyethyl cellulose (2000 CPS at 1%); isopropyl alcohol; coco diethanolamide; triclosan

FIKES Foaming Anti-Microbial Food Service Hand Wash

Drug Facts

Active Ingredient:

Chloroxylenol (1.49% w/w)

Purpose:

Anti-Microbial Hand Cleanser

Uses

- Helps reduce bacteria that potentially can cause disease
- Helps prevent cross contamination by hand contact

Warnings

- For external use only

- Keep out of reach of children. In case of eye contact flush with water for 15 minutes. If irritation persists, get medical attention. In case of accidental ingestion, seek medical attention or contact a poison control center immediately.
- This product must be dispensed from an adequate dispenser located a sufficient distance from processing line to prevent accidental product contamination.
- Do not contaminate water, food or feed by storage and disposal.

Directions

- Apply cleaner to palm of hand
- Lather and scrub hands (including fingers, wrist, and cuticles) vigorously for 60 seconds
- Rinse with water until all cleaner is removed from hands
- Dry completely (incomplete drying may lead to chapped skin).

Inactive Ingredients

Water, 2-Propanol, Sodium Laureth Sulfate, Cocoamidopropyl Betaine, Cocoamphoproprionate,
Cocoamide, Hydroxyethyl Cellulose, Triclosan, FD&C Yellow #5, FD&C Red #40.

The container is coded for Recycling

510-003-100-501

Manufactured for:
Fikes Northwest, Corp.
13401 E. Trent Ave., Spokane Valley, WA 99216
(509) 926-0534 • (509) 755-0370 Fax
fikesnw@att.net • www.fikesnorthwest.com

Principal Display Panel - Bottle Label

Bottle Label:

FIKES

Foaming Anti-Microbial

Food Service Hand Wash

An Anti-Microbial Lotion Hand Wash

Formulated To Clean Effectively,

Yet Gently. Reduces Total Cost Per Hand Wash

Keep Out Of Reach Of Children

CAUTION

See back panel for additional precautionary information.